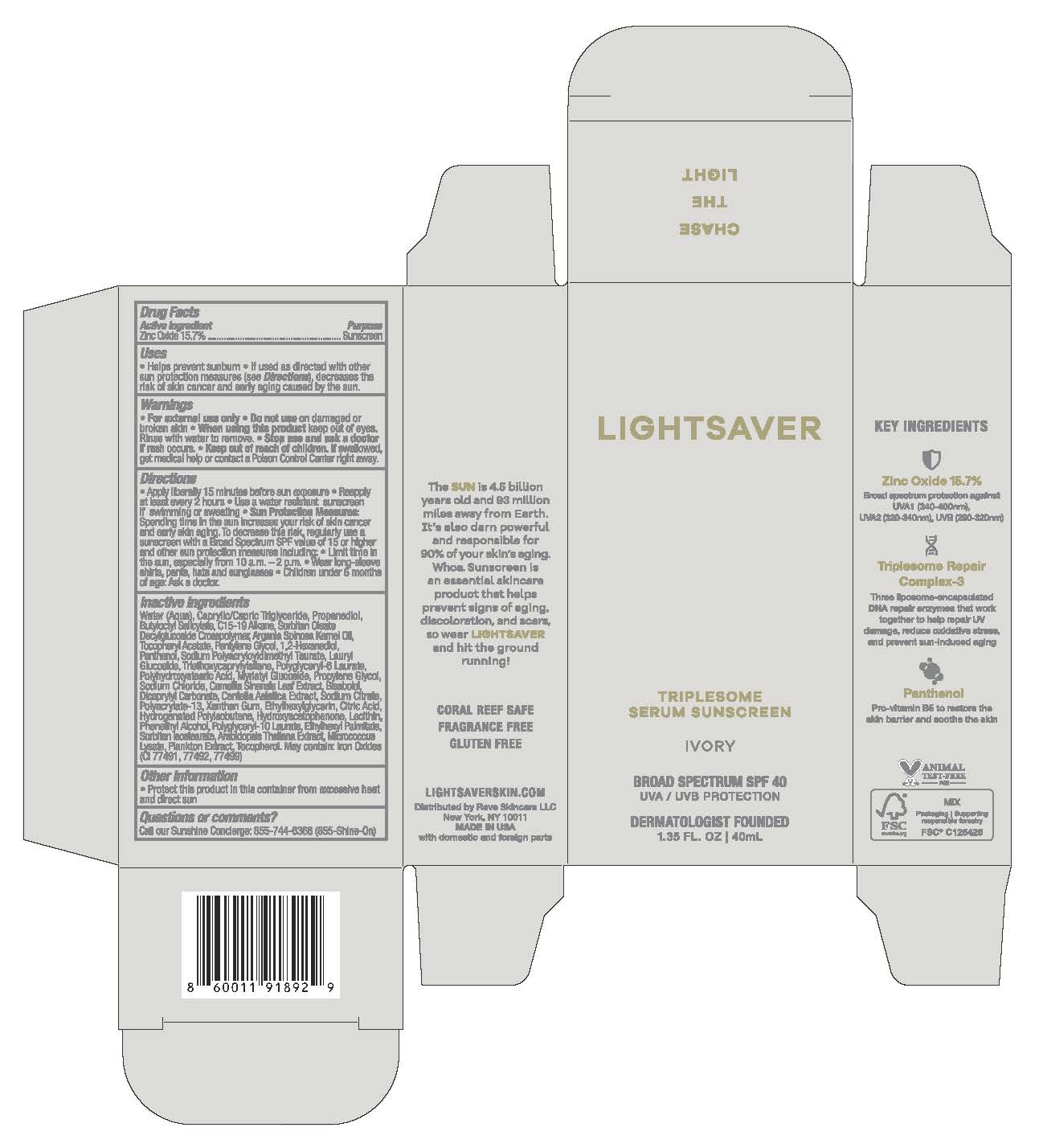 DRUG LABEL: LIGHTSAVE TRIPLESOME SERUM IVORTY
NDC: 83083-010 | Form: CREAM
Manufacturer: Reve Skincare LLC
Category: otc | Type: HUMAN OTC DRUG LABEL
Date: 20251204

ACTIVE INGREDIENTS: ZINC OXIDE 15.7 mg/1 mL
INACTIVE INGREDIENTS: ETHYLHEXYL PALMITATE; ARABIDOPSIS THALIANA WHOLE; WATER; CAPRYLIC/CAPRIC TRIGLYCERIDE; BUTYLOCTYL SALICYLATE; PROPANEDIOL; C15-19 ALKANE; ARGANIA SPINOSA KERNEL OIL; 1,2-HEXANEDIOL; SORBITAN OLEATE DECYLGLUCOSIDE CROSSPOLYMER; PENTYLENE GLYCOL; PANTHENOL; SODIUM POLYACRYLOYLDIMETHYL TAURATE; LAURYL GLUCOSIDE; TRIETHOXYCAPRYLYLSILANE; POLYGLYCERYL-6 LAURATE; POLYHYDROXYSTEARIC ACID (2300 MW); ISOSTEARIC ACID; POLYGLYCERYL-3 PENTARICINOLEATE; MYRISTYL GLUCOSIDE; SODIUM CHLORIDE; XANTHAN GUM; CAMELLIA SINENSIS LEAF; BISABOLOL; DICAPRYLYL CARBONATE; CENTELLA ASIATICA WHOLE; SODIUM CITRATE; ETHYLHEXYLGLYCERIN; CITRIC ACID; HYDROGENATED POLYBUTENE (1300 MW); HYDROXYACETOPHENONE; LECITHIN, SOYBEAN; PHENETHYL ALCOHOL; POLYGLYCERYL-10 LAURATE; BROWN IRON OXIDE; TOCOPHEROL; SORBITAN ISOSTEARATE

Reve Lightsaver Ivory

Active Ingredients

Zinc Oxide 15.7%

Uses

• helps prevent sunburn • if used as directed with other
sun protection measures (see Directions), decreases the
risk of skin cancer and early skin aging caused by the sun

Warnings

For external use only
Do not use on damaged or broken skin.
When using this product keep out of eyes. Rinse with water to remove.
Stop use and ask a docor if rash occurs
Keep out of reach of children. If swalled, get medical help or contact a Poison Control Center right away.

Directions

• apply generously 15 minutes before sun exposure
• reapply: •at least every 2 hours.

• use a water resistant sunscreen if swimming or sweating
• Sun Protection Measures. Spending time in the sun

increases your risk of skin cancer and early skin aging. To decrease
this risk, regularly use a sunscreen with a Broad Spectrum SPF
value of 15 or higher and other sun protection measures including:
• limit time in the sun, especially from 10 a.m. - 2 p.m.
• wear long-sleeved shirts, pants, hats, and sunglasses
• children under 6 months of age: Ask a doctor

Inactive ingredients

Water (Aqua), Caprylic/Capric Triglyceride, Propanediol, Butyloctyl Salicylate, C15-19 Alkane, Sorbitan Oleate Decylglucoside Crosspolymer, Argania Spinosa Kernel Oil, Tocopheryl Acetate, Pentylene Glycol, 1,2-Hexanediol, Panthenol, Sodium Polyacryloyldimethyl Taurate, Lauryl Glucoside, Triethoxycaprylylsilane, Polyglyceryl-6 Laurate, Polyhydroxystearic Acid, Myristyl Glucoside, Propylene Glycol, Sodium Chloride, Camellia Sinensis Leaf Extract, Bisabolol, Dicaprylyl Carbonate, Centella Asiatica Extract, Sodium Citrate, Polyacrylate-13, Xanthan Gum, Ethylhexylglycerin, Citric Acid, Hydrogenated Polyisobutene, Hydroxyacetophenone, Lecithin, Phenethyl Alcohol, Polyglyceryl-10 Laurate, Ethylhexyl Palmitate, Sorbitan Isostearate, Arabidopsis Thaliana Extract, Micrococcus Lysate, Plankton Extract, Tocopherol. May Contain: Iron Oxides (CI 77491, 77492, 77499)

Other Information

• protect the product in this container from excessive
heat and direct sun

Questions or Comments?

Call our Sunshine Concierge: 855-744-6366 (855-Shine-On)

Purpose

Sunscreen

Keep out of reach of children.

Topical